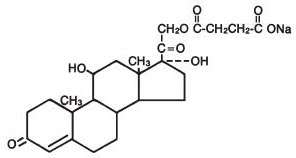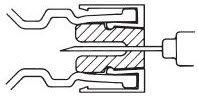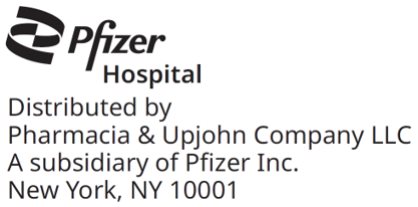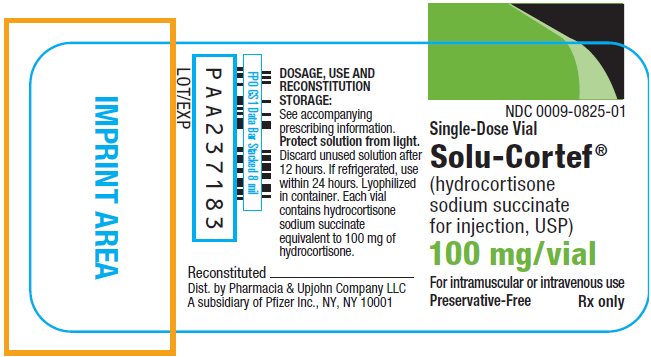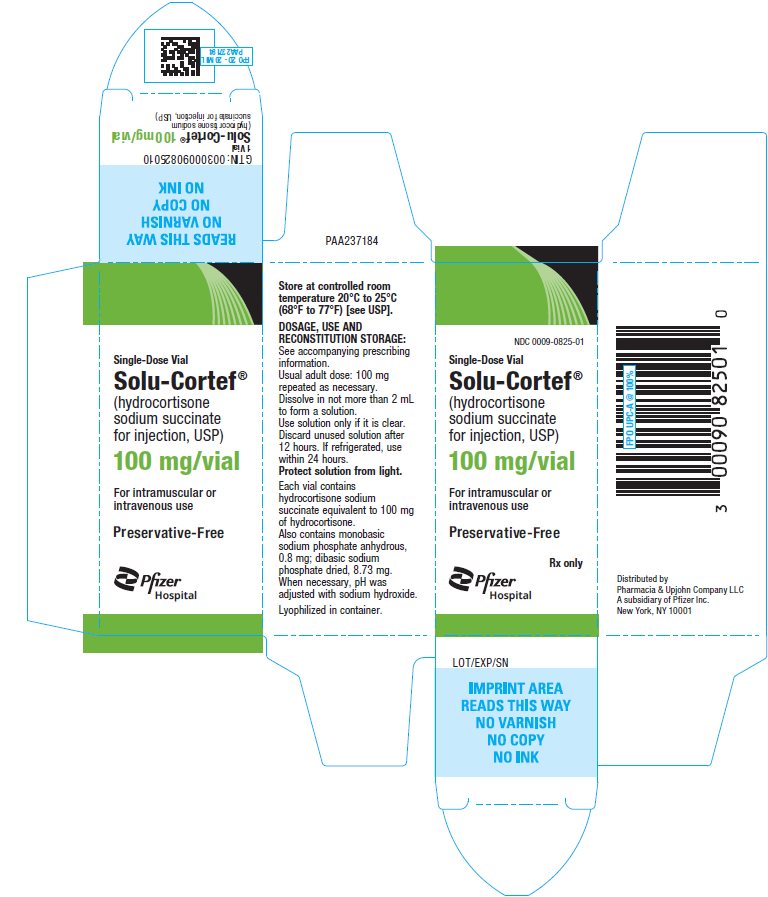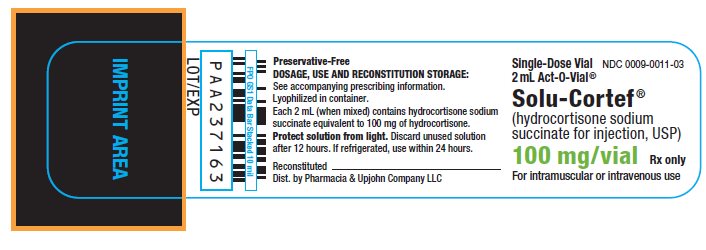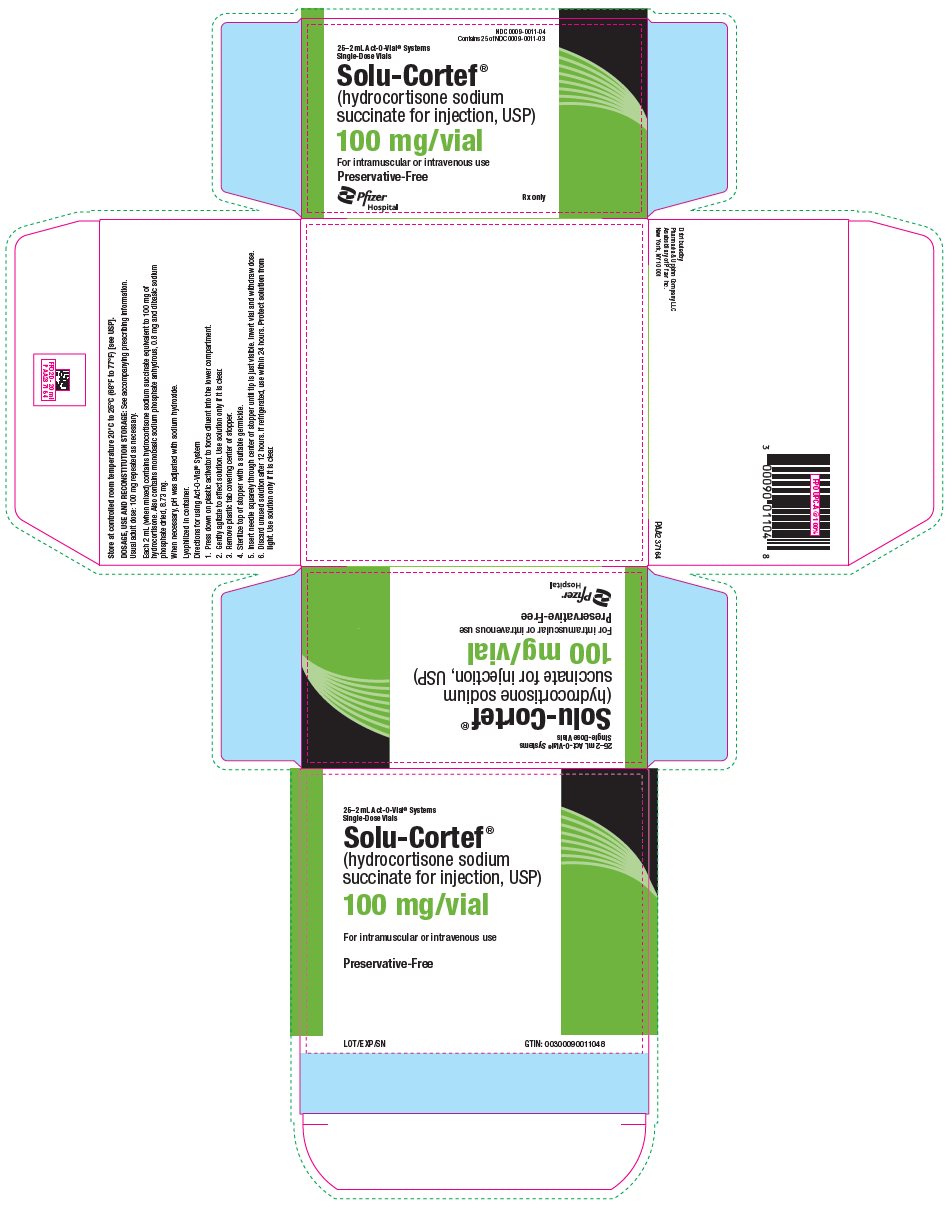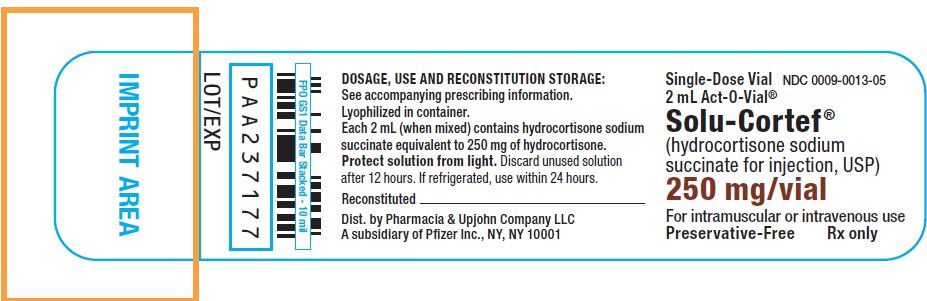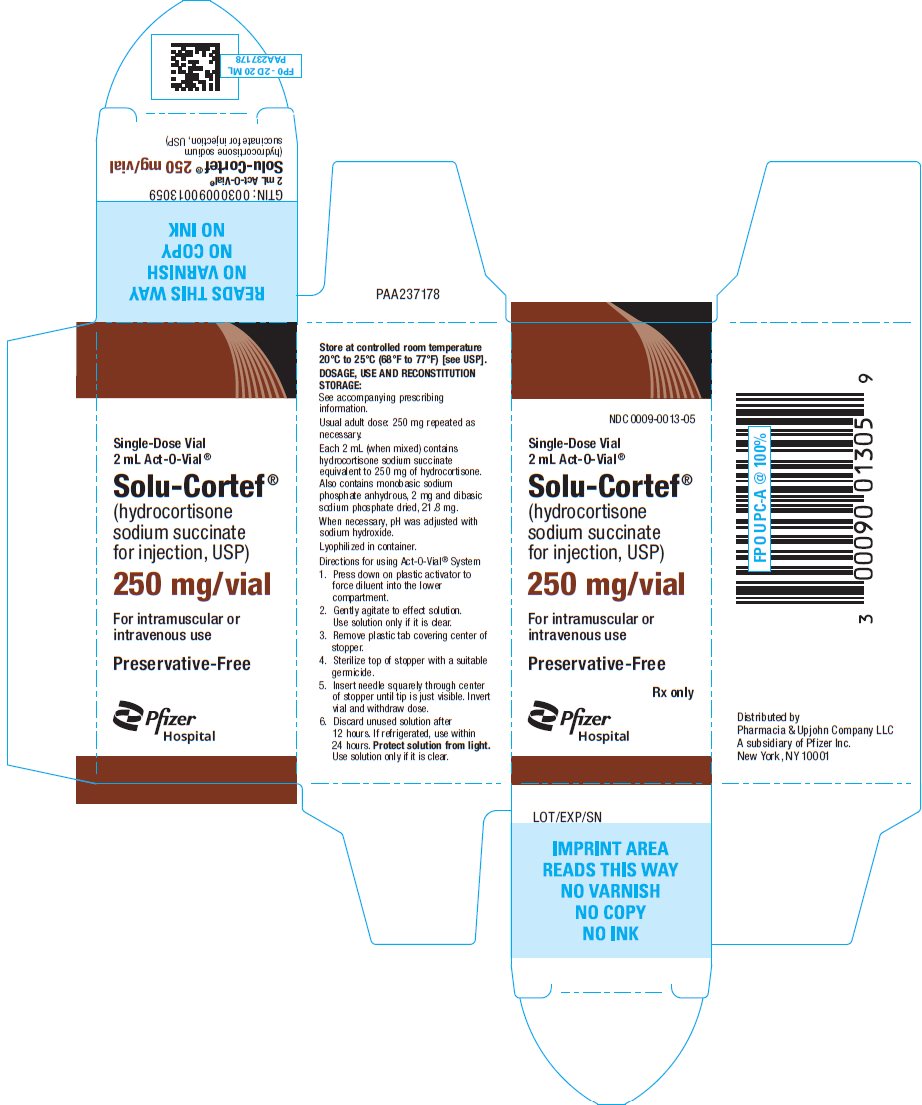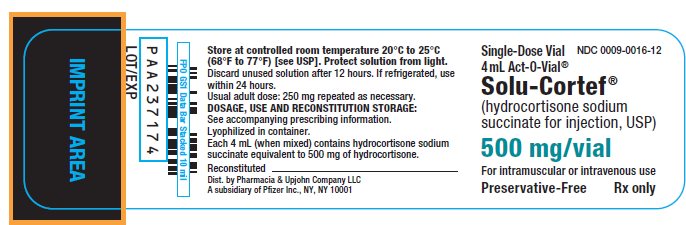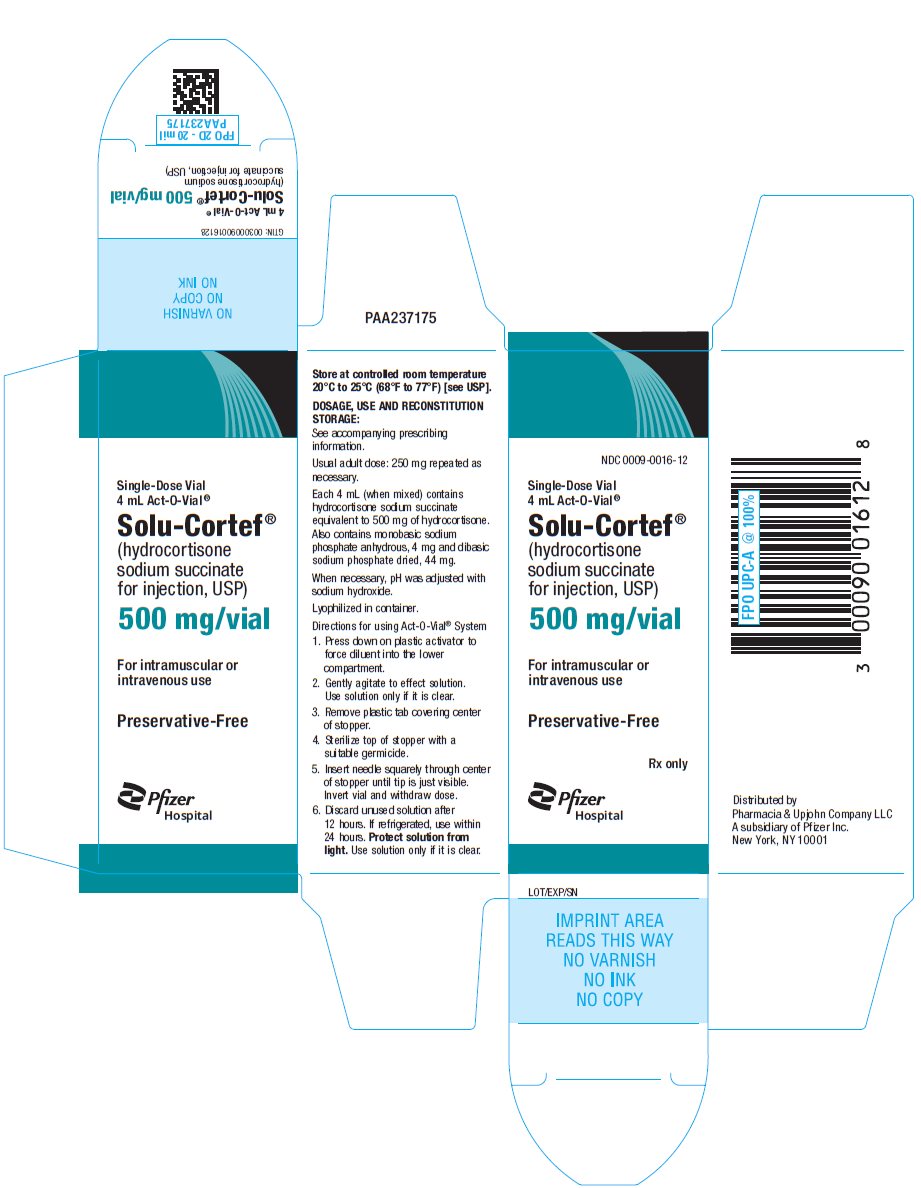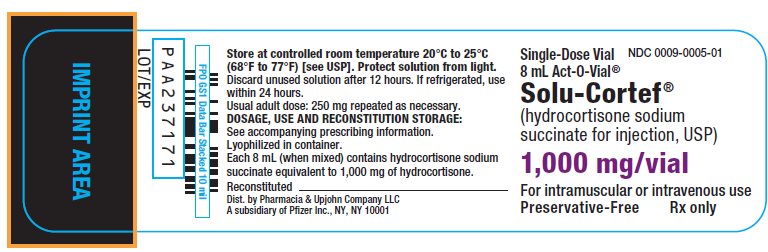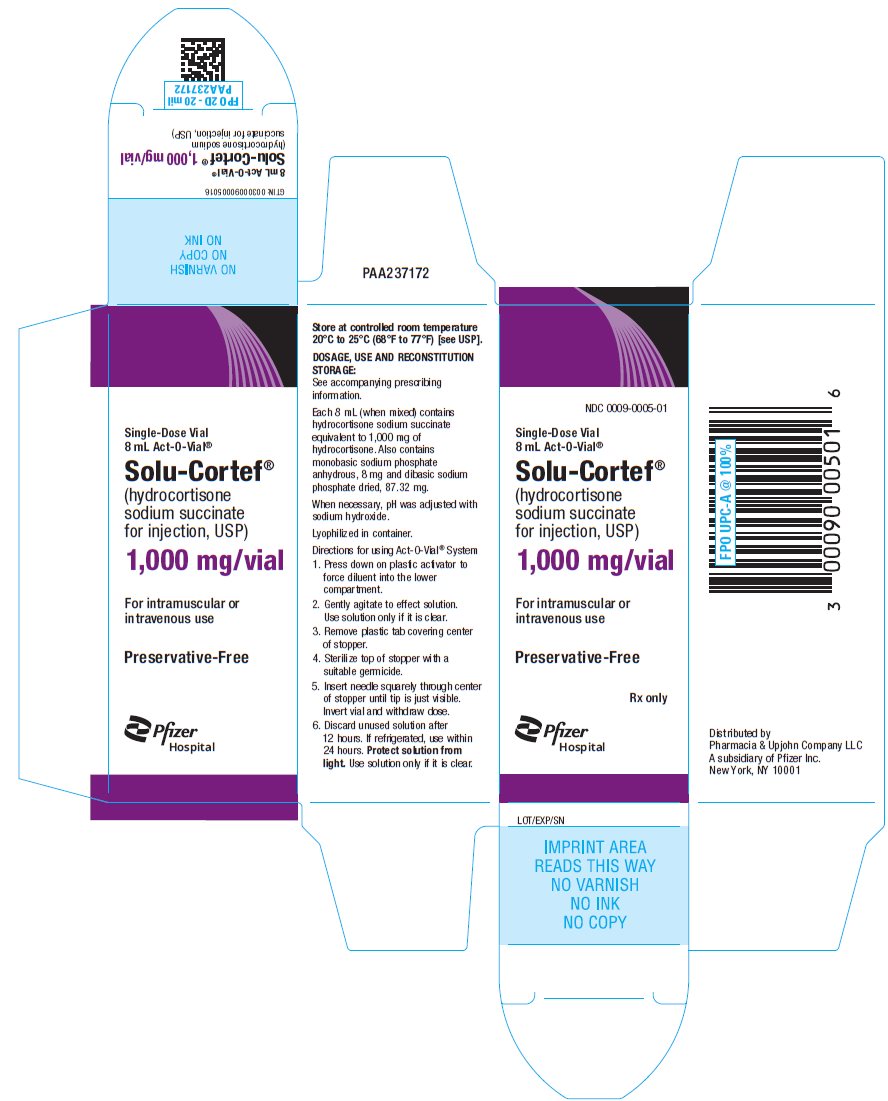 DRUG LABEL: Solu-Cortef
NDC: 0009-0825 | Form: INJECTION, POWDER, FOR SOLUTION
Manufacturer: Pharmacia & Upjohn Company LLC
Category: prescription | Type: HUMAN PRESCRIPTION DRUG LABEL
Date: 20250905

ACTIVE INGREDIENTS: HYDROCORTISONE SODIUM SUCCINATE 100 mg/2 mL
INACTIVE INGREDIENTS: SODIUM PHOSPHATE, MONOBASIC, ANHYDROUS 0.8 mg/2 mL; SODIUM PHOSPHATE, DIBASIC, UNSPECIFIED FORM 8.73 mg/2 mL

SOLU-CORTEF®
(hydrocortisone sodium succinate for injection, USP)

For Intravenous or Intramuscular Administration

DESCRIPTION

SOLU-CORTEF Sterile Powder is an anti-inflammatory glucocorticoid that contains hydrocortisone sodium succinate as the active ingredient. SOLU-CORTEF Sterile Powder is available in several packages for intravenous or intramuscular administration.

100 mg Plain

Vials containing hydrocortisone sodium succinate equivalent to 100 mg hydrocortisone, 0.8 mg monobasic sodium phosphate anhydrous, 8.73 mg dibasic sodium phosphate dried. SOLU-CORTEF 100 mg plain does not contain diluent (see DOSAGE AND ADMINISTRATION, Preparation of Solutions).

ACT-O-VIAL® System (Single-Dose Vial) in four strengths:
 | 100 mg ACT-O-VIAL | 250 mg ACT-O-VIAL | 500 mg ACT-O-VIAL | 1,000 mg ACT-O-VIAL
 | Each 2 mL contains (when mixed): | Each 2 mL contains (when mixed): | Each 4 mL contains (when mixed): | Each 8 mL contains (when mixed):
Hydrocortisone sodium succinate | equiv. to 100 mg Hydrocortisone | equiv. to 250 mg Hydrocortisone | equiv. to 500 mg Hydrocortisone | equiv. to 1,000 mg Hydrocortisone
Monobasic sodium phosphate anhydrous | 0.8 mg | 2 mg | 4 mg | 8 mg
Dibasic sodium phosphate dried | 8.73 mg | 21.8 mg | 44 mg | 87.32 mg

The diluent, as part of the packaging presentation for the ACT-O-VIAL® system, is comprised of Water for Injection only, and does not contain any preservative.

When necessary, the pH of each formula was adjusted with sodium hydroxide so that the pH of the reconstituted solution is within the USP specified range of 7 to 8.

The chemical name for hydrocortisone sodium succinate is pregn-4-ene-3,20-dione,21-(3-carboxy-1-oxopropoxy)-11,17-dihydroxy-, monosodium salt, (11β)- and its molecular weight is 484.52.

The structural formula is represented below:

Hydrocortisone sodium succinate is a white or nearly white, odorless, hygroscopic amorphous solid. It is very soluble in water and in alcohol, very slightly soluble in acetone, and insoluble in chloroform.

CLINICAL PHARMACOLOGY

Glucocorticoids, naturally occurring and synthetic, are adrenocortical steroids that are readily absorbed from the gastrointestinal tract.

Naturally occurring glucocorticoids (hydrocortisone and cortisone), which also have salt-retaining properties, are used as replacement therapy in adrenocortical deficiency states. Their synthetic analogs are primarily used for their anti-inflammatory effects in disorders of many organ systems.

Hydrocortisone sodium succinate has the same metabolic and anti-inflammatory actions as hydrocortisone. When given parenterally and in equimolar quantities, the two compounds are equivalent in biologic activity. The highly water-soluble sodium succinate ester of hydrocortisone permits the immediate intravenous administration of high doses of hydrocortisone in a small volume of diluent and is particularly useful where high blood levels of hydrocortisone are required rapidly. Following the intravenous injection of hydrocortisone sodium succinate, demonstrable effects are evident within one hour and persist for a variable period. Excretion of the administered dose is nearly complete within 12 hours. Thus, if constantly high blood levels are required, injections should be made every 4 to 6 hours. This preparation is also rapidly absorbed when administered intramuscularly and is excreted in a pattern similar to that observed after intravenous injection.

Glucocorticoids cause profound and varied metabolic effects. In addition, they modify the body's immune response to diverse stimuli.

INDICATIONS AND USAGE

When oral therapy is not feasible, and the strength, dosage form, and route of administration of the drug reasonably lend the preparation to the treatment of the condition, the intravenous or intramuscular use of SOLU-CORTEF Sterile Powder is indicated as follows:

Allergic states: Control of severe or incapacitating allergic conditions intractable to adequate trials of conventional treatment in asthma, atopic dermatitis, contact dermatitis, drug hypersensitivity reactions, serum sickness, transfusion reactions.

Dermatologic diseases: Bullous dermatitis herpetiformis, exfoliative erythroderma, mycosis fungoides, pemphigus, severe erythema multiforme (Stevens-Johnson syndrome).

Endocrine disorders: Primary or secondary adrenocortical insufficiency (hydrocortisone or cortisone is the drug of choice; synthetic analogs may be used in conjunction with mineralocorticoids where applicable; in infancy, mineralocorticoid supplementation is of particular importance), congenital adrenal hyperplasia, hypercalcemia associated with cancer, nonsuppurative thyroiditis.

Gastrointestinal diseases: To tide the patient over a critical period of the disease in regional enteritis (systemic therapy) and ulcerative colitis.

Hematologic disorders: Acquired (autoimmune) hemolytic anemia, congenital (erythroid) hypoplastic anemia (Diamond Blackfan anemia), idiopathic thrombocytopenic purpura in adults (intravenous administration only; intramuscular administration is contraindicated), pure red cell aplasia, select cases of secondary thrombocytopenia.

Miscellaneous: Trichinosis with neurologic or myocardial involvement, tuberculous meningitis with subarachnoid block or impending block when used concurrently with appropriate antituberculous chemotherapy.

Neoplastic diseases: For the palliative management of leukemias and lymphomas.

Nervous System: Cerebral edema associated with primary or metastatic brain tumor, or craniotomy.

Ophthalmic diseases: Sympathetic ophthalmia, uveitis and ocular inflammatory conditions unresponsive to topical corticosteroids.

Renal diseases: To induce diuresis or remission of proteinuria in idiopathic nephrotic syndrome, or that due to lupus erythematosus.

Respiratory diseases: Berylliosis, fulminating or disseminated pulmonary tuberculosis when used concurrently with appropriate antituberculous chemotherapy, idiopathic eosinophilic pneumonias, symptomatic sarcoidosis.

Rheumatic disorders: As adjunctive therapy for short-term administration (to tide the patient over an acute episode or exacerbation) in acute gouty arthritis; acute rheumatic carditis; ankylosing spondylitis; psoriatic arthritis; rheumatoid arthritis, including juvenile rheumatoid arthritis (selected cases may require low-dose maintenance therapy). For the treatment of dermatomyositis, temporal arteritis, polymyositis, and systemic lupus erythematosus.

CONTRAINDICATIONS

SOLU-CORTEF Sterile Powder is contraindicated in systemic fungal infections and patients with known hypersensitivity to the product and its constituents.

Intramuscular corticosteroid preparations are contraindicated for idiopathic thrombocytopenic purpura.

SOLU-CORTEF Sterile Powder is contraindicated for intrathecal administration. Reports of severe medical events have been associated with this route of administration.

WARNINGS

Serious Neurologic Adverse Reactions with Epidural Administration:

Serious neurologic events, some resulting in death, have been reported with epidural injection of corticosteroids. Specific events reported include, but are not limited to, spinal cord infarction, paraplegia, quadriplegia, cortical blindness, and stroke. These serious neurologic events have been reported with and without use of fluoroscopy. The safety and effectiveness of epidural administration of corticosteroids have not been established, and corticosteroids are not approved for this use.

General:

Injection of SOLU-CORTEF may result in dermal and/or subdermal changes forming depressions in the skin at the injection site. In order to minimize the incidence of dermal and subdermal atrophy, care must be exercised not to exceed recommended doses in injections. Injection into the deltoid muscle should be avoided because of a high incidence of subcutaneous atrophy.

Rare instances of anaphylactoid reactions have occurred in patients receiving corticosteroid therapy (see ADVERSE REACTIONS).

Increased dosage of rapidly acting corticosteroids is indicated in patients on corticosteroid therapy subjected to any unusual stress before, during, and after the stressful situation.

Results from one multicenter, randomized, placebo-controlled study with methylprednisolone hemisuccinate, an IV corticosteroid, showed an increase in early (at 2 weeks) and late (at 6 months) mortality in patients with cranial trauma who were determined not to have other clear indications for corticosteroid treatment. High doses of systemic corticosteroids, including SOLU-CORTEF, should not be used for the treatment of traumatic brain injury.

Cardio-renal:

Average and large doses of corticosteroids can cause elevation of blood pressure, salt and water retention, and increased excretion of potassium. These effects are less likely to occur with the synthetic derivatives except when used in large doses. Dietary salt restriction and potassium supplementation may be necessary. All corticosteroids increase calcium excretion.

Literature reports suggest an apparent association between use of corticosteroids and left ventricular free wall rupture after a recent myocardial infarction; therefore, therapy with corticosteroids should be used with great caution in these patients.

There have been cases reported in which concomitant use of amphotericin B and hydrocortisone was followed by cardiac enlargement and congestive heart failure (see CONTRAINDICATIONS and PRECAUTIONS: Drug Interactions, Amphotericin B injection and potassium-depleting agents).

Endocrine:

Hypothalamic-pituitary adrenal (HPA) axis suppression, Cushing's syndrome, and hyperglycemia. Monitor patients for these conditions with chronic use. Corticosteroids can produce reversible HPA axis suppression with the potential for glucocorticosteroid insufficiency after withdrawal of treatment. Drug induced secondary adrenocortical insufficiency may be minimized by gradual reduction of dosage. This type of relative insufficiency may persist for months after discontinuation of therapy; therefore, in any situation of stress occurring during that period, hormone therapy should be reinstituted.

Immunosuppression and Increased Risk of Infection

Corticosteroids, including SOLU-CORTEF, suppress the immune system and increase the risk of infection with any pathogen, including viral, bacterial, fungal, protozoan, or helminthic pathogens. Corticosteroids can:

- Reduce resistance to new infections
- Exacerbate existing infections
- Increase the risk of disseminated infections
- Increase the risk of reactivation or exacerbation of latent infections
- Mask some signs of infection

Corticosteroid-associated infections can be mild but can be severe and at times fatal. The rate of infectious complications increases with increasing corticosteroid dosages.

Monitor for the development of infection and consider SOLU-CORTEF withdrawal or dosage reduction as needed. Do not administer SOLU-CORTEF by an intraarticular, intrabursal, or intratendinous route in the presence of acute local infection.

Tuberculosis

If SOLU-CORTEF is used to treat a condition in patients with latent tuberculosis or tuberculin reactivity, reactivation of the disease may occur. Closely monitor such patients for reactivation. During prolonged SOLU-CORTEF therapy, patients with latent tuberculosis or tuberculin reactivity should receive chemoprophylaxis.

Varicella Zoster and Measles Viral Infections

Varicella and measles can have a serious or even fatal course in non-immune patients taking corticosteroids. In corticosteroid-treated patients who have not had these diseases or are nonimmune, particular care should be taken to avoid exposure to varicella and measles:

- If a SOLU-CORTEF-treated patient is exposed to varicella, prophylaxis with varicella zoster immune globulin (VZIG) may be indicated. If varicella develops, treatment with antiviral agents may be considered.
- If a SOLU-CORTEF-treated patient is exposed to measles, prophylaxis with immunoglobulin (IG) may be indicated.

Hepatitis B Virus Reactivation

Hepatitis B virus reactivation can occur in patients who are hepatitis B carriers treated with immunosuppressive dosages of corticosteroids, including SOLU-CORTEF. Reactivation can also occur infrequently in corticosteroid-treated patients who appear to have resolved hepatitis B infection.

Screen patients for hepatitis B infection before initiating immunosuppressive (e.g., prolonged) treatment with SOLU-CORTEF. For patients who show evidence of hepatitis B infection, recommend consultation with physicians with expertise in managing hepatitis B regarding monitoring and consideration for hepatitis B antiviral therapy.

Fungal Infections

Corticosteroids, including SOLU-CORTEF, may exacerbate systemic fungal infections; therefore, avoid SOLU-CORTEF use in the presence of such infections unless SOLU-CORTEF is needed to control drug reactions. For patients on chronic SOLU-CORTEF therapy who develop systemic fungal infections, SOLU-CORTEF withdrawal or dosage reduction is recommended.

Amebiasis

Corticosteroids, including SOLU-CORTEF, may activate latent amebiasis. Therefore, it is recommended that latent amebiasis or active amebiasis be ruled out before initiating SOLU-CORTEF in patients who have spent time in the tropics or patients with unexplained diarrhea.

Strongyloides Infestation

Corticosteroids, including SOLU-CORTEF, should be used with great care in patients with known or suspected Strongyloides (threadworm) infestation. In such patients, corticosteroid-induced immunosuppression may lead to Strongyloides hyperinfection and dissemination with widespread larval migration, often accompanied by severe enterocolitis and potentially fatal gram-negative septicemia.

Cerebral Malaria

Avoid corticosteroids, including SOLU-CORTEF, in patients with cerebral malaria.

Vaccination:

Administration of live or live, attenuated vaccines is contraindicated in patients receiving immunosuppressive doses of corticosteroids. Killed or inactivated vaccines may be administered. However, the response to such vaccines cannot be predicted. Immunization procedures may be undertaken in patients who are receiving corticosteroids as replacement therapy (e.g., for Addison’s disease).

Neurologic:

Reports of severe medical events have been associated with the intrathecal route of administration (see ADVERSE REACTIONS, Neurologic/Psychiatric).

Ophthalmic:

Use of corticosteroids may produce posterior subcapsular cataracts, glaucoma with possible damage to the optic nerves, and may enhance the establishment of secondary ocular infections due to bacteria, fungi, or viruses. The use of oral corticosteroids is not recommended in the treatment of optic neuritis and may lead to an increase in the risk of new episodes. Corticosteroids should be used cautiously in patients with ocular herpes simplex because of corneal perforation. Corticosteroids should not be used in active ocular herpes simplex.

Kaposi’s Sarcoma:

Kaposi's sarcoma has been reported to occur in patients receiving corticosteroid therapy, most often for chronic conditions. Discontinuation of corticosteroids may result in clinical improvement of Kaposi’s sarcoma.

PRECAUTIONS

General:

The lowest possible dose of corticosteroid should be used to control the condition under treatment. When reduction in dosage is possible, the reduction should be gradual.

Since complications of treatment with glucocorticoids are dependent on the size of the dose and the duration of treatment, a risk/benefit decision must be made in each individual case as to dose and duration of treatment and as to whether daily or intermittent therapy should be used.

Cardio-renal:

As sodium retention with resultant edema and potassium loss may occur in patients receiving corticosteroids, these agents should be used with caution in patients with congestive heart failure, hypertension, or renal insufficiency.

Endocrine:

Drug-induced secondary adrenocortical insufficiency may be minimized by gradual reduction of dosage. This type of relative insufficiency may persist for months after discontinuation of therapy; therefore, in any situation of stress occurring during that period, hormone therapy should be reinstituted. Metabolic clearance of corticosteroids is decreased in hypothyroid patients and increased in hyperthyroid patients. Changes in thyroid status of the patient may necessitate adjustment in dosage.

Gastrointestinal:

Steroids should be used with caution in active or latent peptic ulcers, diverticulitis, fresh intestinal anastomoses, and non-specific ulcerative colitis, since they may increase the risk of a perforation. Signs of peritoneal irritation following gastrointestinal perforation in patients receiving corticosteroids may be minimal or absent.

There is an enhanced effect due to decreased metabolism of corticosteroids in patients with cirrhosis.

Musculoskeletal:

Corticosteroids decrease bone formation and increase bone resorption both through their effect on calcium regulation (e.g., decreasing absorption and increasing excretion) and inhibition of osteoblast function. This, together with a decrease in the protein matrix of the bone secondary to an increase in protein catabolism, and reduced sex hormone production, may lead to inhibition of bone growth in pediatric patients and the development of osteoporosis at any age. Special consideration should be given to patients at increased risk of osteoporosis (i.e., postmenopausal women) before initiating corticosteroid therapy.

Local injection of a steroid into a previously infected site is not usually recommended.

Neurologic-psychiatric:

An acute myopathy has been observed with the use of high doses of corticosteroids, most often occurring in patients with disorders of neuromuscular transmission (e.g., myasthenia gravis), or in patients receiving concomitant therapy with neuromuscular blocking drugs (e.g., pancuronium). This acute myopathy is generalized, may involve ocular and respiratory muscles, and may result in quadriparesis. Elevation of creatine kinase may occur. Clinical improvement or recovery after stopping corticosteroids may require weeks to years.

Psychic derangements may appear when corticosteroids are used, ranging from euphoria, insomnia, mood swings, personality changes, and severe depression to frank psychotic manifestations. Also, existing emotional instability or psychotic tendencies may be aggravated by corticosteroids.

Ophthalmic:

Intraocular pressure may become elevated in some individuals. If steroid therapy is continued for more than 6 weeks, intraocular pressure should be monitored.

Other:

Pheochromocytoma crisis, which can be fatal, has been reported after administration of systemic corticosteroids. In patients with suspected pheochromocytoma, consider the risk of pheochromocytoma crisis prior to administering corticosteroids.

Tumor Lysis Syndrome:

In post marketing experience tumor lysis syndrome (TLS) has been reported in patients with malignancies, including hematological malignancies and solid tumors, following the use of systemic corticosteroids alone or in combination with other chemotherapeutic agents. Patients at high risk of TLS, such as patients with tumors that have a high proliferative rate, high tumor burden and high sensitivity to cytotoxic agents, should be monitored closely and appropriate precautions should be taken.

Information for Patients:

Patients should be warned not to discontinue the use of corticosteroids abruptly or without medical supervision, to advise any medical attendants that they are taking corticosteroids, and to seek medical advice at once should they develop fever or other signs of infection.

Persons who are on corticosteroids should be warned to avoid exposure to chicken pox or measles. Patients should also be advised that if they are exposed, medical advice should be sought without delay.

Drug Interactions

Aminoglutethimide: Aminoglutethimide may lead to a loss of corticosteroid-induced adrenal suppression. Amphotericin B injection and potassium-depleting agents: When corticosteroids are administered concomitantly with potassium-depleting agents (e.g., amphotericin B, diuretics), patients should be observed closely for development of hypokalemia. There have been cases reported in which concomitant use of amphotericin B and hydrocortisone was followed by cardiac enlargement and congestive heart failure.

Antibiotics: Macrolide antibiotics have been reported to cause a significant decrease in corticosteroid clearance (see PRECAUTIONS: Drug Interactions, Hepatic Enzyme Inhibitors).

Anticholinesterases: Concomitant use of anticholinesterase agents and corticosteroids may produce severe weakness in patients with myasthenia gravis. If possible, anticholinesterase agents should be withdrawn at least 24 hours before initiating corticosteroid therapy.

Anticoagulants, oral: Coadministration of corticosteroids and warfarin usually results in inhibition of response to warfarin, although there have been some conflicting reports. Therefore, coagulation indices should be monitored frequently to maintain the desired anticoagulant effect.

Antidiabetics: Because corticosteroids may increase blood glucose concentrations, dosage adjustments of antidiabetic agents may be required.

Antitubercular drugs: Serum concentrations of isoniazid may be decreased.

Cholestyramine: Cholestyramine may increase the clearance of corticosteroids.

Cyclosporine: Increased activity of both cyclosporine and corticosteroids may occur when the two are used concurrently. Convulsions have been reported with this concurrent use.

Digitalis glycosides: Patients on digitalis glycosides may be at increased risk of arrhythmias due to hypokalemia.

Estrogens, including oral contraceptives: Estrogens may decrease the hepatic metabolism of certain corticosteroids, thereby increasing their effect.

Hepatic Enzyme Inducers (e.g., barbiturates, phenytoin, carbamazepine, rifampin): Drugs that induce cytochrome P450 3A4 enzyme activity may enhance the metabolism of corticosteroids and require that the dosage of the corticosteroid be increased.

Hepatic Enzyme Inhibitors (e.g., ketoconazole, macrolide antibiotics such as erythromycin and troleandomycin): Drugs that inhibit cytochrome P450 3A4 have the potential to result in increased plasma concentrations of corticosteroids.

Ketoconazole: Ketoconazole has been reported to significantly decrease the metabolism of certain corticosteroids by up to 60%, leading to an increased risk of corticosteroid side effects.

Nonsteroidal anti-inflammatory drugs (NSAIDs): Concomitant use of aspirin (or other nonsteroidal anti-inflammatory agents) and corticosteroids increases the risk of gastrointestinal side effects. Aspirin should be used cautiously in conjunction with corticosteroids in hypoprothrombinemia. The clearance of salicylates may be increased with concurrent use of corticosteroids.

Skin tests: Corticosteroids may suppress reactions to skin tests.

Vaccines: Patients on prolonged corticosteroid therapy may exhibit a diminished response to toxoids and live or inactivated vaccines due to inhibition of antibody response. Corticosteroids may also potentiate the replication of some organisms contained in live attenuated vaccines. Routine administration of vaccines or toxoids should be deferred until corticosteroid therapy is discontinued if possible (see WARNINGS: Immunosuppression and Increased Risk of Infection, Vaccination).

Carcinogenesis, Mutagenesis, Impairment of Fertility:

No adequate studies have been conducted in animals to determine whether corticosteroids have a potential for carcinogenesis or mutagenesis.

Steroids may increase or decrease motility and number of spermatozoa in some patients.

Corticosteroids have been shown to impair fertility in male rats.

Pregnancy:

Teratogenic Effects

Corticosteroids have been shown to be teratogenic in many species when given in doses equivalent to the human dose. Animal studies in which corticosteroids have been given to pregnant mice, rats, and rabbits have yielded an increased incidence of cleft palate in the offspring. There are no adequate and well-controlled studies in pregnant women. Corticosteroids should be used during pregnancy only if the potential benefit justifies the potential risk to the fetus. Infants born to mothers who have received corticosteroids during pregnancy should be carefully observed for signs of hypoadrenalism.

Nursing Mothers:

Systemically administered corticosteroids appear in human milk and could suppress growth, interfere with endogenous corticosteroid production, or cause other untoward effects. Because of the potential for serious adverse reactions in nursing infants from corticosteroids, a decision should be made whether to continue nursing or discontinue the drug, taking into account the importance of the drug to the mother.

Pediatric Use:

The efficacy and safety of corticosteroids in the pediatric population are based on the well-established course of effect of corticosteroids, which is similar in pediatric and adult populations. Published studies provide evidence of efficacy and safety in pediatric patients for the treatment of nephrotic syndrome (>2 years of age) and aggressive lymphomas and leukemias (>1 month of age). Other indications for pediatric use of corticosteroids (e.g., severe asthma and wheezing) are based on adequate and well-controlled trials conducted in adults, on the premises that the course of the diseases and their pathophysiology are considered to be substantially similar in both populations.

The adverse effects of corticosteroids in pediatric patients are similar to those in adults (see ADVERSE REACTIONS). Like adults, pediatric patients should be carefully observed with frequent measurements of blood pressure, weight, height, intraocular pressure, and clinical evaluation for the presence of infection, psychosocial disturbances, thromboembolism, peptic ulcers, cataracts, and osteoporosis. Pediatric patients who are treated with corticosteroids by any route, including systemically administered corticosteroids, may experience a decrease in their growth velocity. This negative impact of corticosteroids on growth has been observed at low systemic doses and in the absence of laboratory evidence of HPA axis suppression (i.e., cosyntropin stimulation and basal cortisol plasma levels). Growth velocity may therefore be a more sensitive indicator of systemic corticosteroid exposure in pediatric patients than some commonly used tests of HPA axis function. The linear growth of pediatric patients treated with corticosteroids should be monitored, and the potential growth effects of prolonged treatment should be weighed against clinical benefits obtained and the availability of treatment alternatives. In order to minimize the potential growth effects of corticosteroids, pediatric patients should be titrated to the lowest effective dose.

Hypertrophic cardiomyopathy was reported after administration of hydrocortisone to prematurely born infants, therefore appropriate diagnostic evaluation and monitoring of cardiac function and structure should be performed.

Geriatric Use:

Clinical studies did not include sufficient numbers of subjects aged 65 and over to determine whether they respond differently from younger subjects. Other reported clinical experience has not identified differences in responses between the elderly and younger patients. In general, dose selection for an elderly patient should be cautious, usually starting at the low end of the dosing range, reflecting the greater frequency of decreased hepatic, renal, or cardiac function, and of concomitant disease or other drug therapy.

ADVERSE REACTIONS

The following adverse reactions have been reported with SOLU-CORTEF or other corticosteroids:

Allergic reactions: Allergic or hypersensitivity reactions, anaphylactoid reaction, anaphylaxis, angioedema.

Blood and lymphatic system disorders: Leukocytosis.

Cardiovascular: Bradycardia, cardiac arrest, cardiac arrhythmias, cardiac enlargement, circulatory collapse, congestive heart failure, fat embolism, hypertension, hypertrophic cardiomyopathy in premature infants, myocardial rupture following recent myocardial infarction (see WARNINGS), pulmonary edema, syncope, tachycardia, thromboembolism, thrombophlebitis, vasculitis.

Dermatologic: Acne, allergic dermatitis, burning or tingling (especially in the perineal area, after intravenous injection), cutaneous and subcutaneous atrophy, dry scaly skin, ecchymoses and petechiae, edema, erythema, hyperpigmentation, hypopigmentation, impaired wound healing, increased sweating, rash, sterile abscess, striae, suppressed reactions to skin tests, thin fragile skin, thinning scalp hair, urticaria.

Endocrine: Decreased carbohydrate and glucose tolerance, development of cushingoid state, glycosuria, hirsutism, hypertrichosis, increased requirements for insulin or oral hypoglycemic agents in diabetes, manifestations of latent diabetes mellitus, menstrual irregularities, secondary adrenocortical and pituitary unresponsiveness (particularly in times of stress, as in trauma, surgery, or illness), suppression of growth in pediatric patients.

Fluid and electrolyte disturbances: Congestive heart failure in susceptible patients, fluid retention, hypokalemic alkalosis, potassium loss, sodium retention.

Gastrointestinal: Abdominal distention, bowel/bladder dysfunction (after intrathecal administration), elevation in serum liver enzyme levels (usually reversible upon discontinuation), hepatomegaly, increased appetite, nausea, pancreatitis, peptic ulcer with possible perforation and hemorrhage, perforation of the small and large intestine (particularly in patients with inflammatory bowel disease), ulcerative esophagitis.

Metabolic: Negative nitrogen balance due to protein catabolism.

Musculoskeletal: Aseptic necrosis of femoral and humeral heads, Charcot-like arthropathy, loss of muscle mass, muscle weakness, osteoporosis, pathologic fracture of long bones, postinjection flare (following intra-articular use), steroid myopathy, tendon rupture, vertebral compression fractures.

Neurologic/Psychiatric: Convulsions, depression, emotional instability, euphoria, headache, increased intracranial pressure with papilledema (pseudotumor cerebri) usually following discontinuation of treatment, insomnia, mood swings, neuritis, neuropathy, paresthesia, personality changes, psychic disorders, vertigo. Arachnoiditis, meningitis, paraparesis/paraplegia, and sensory disturbances have occurred after intrathecal administration (see WARNINGS: Neurologic), epidural lipomatosis.

Ophthalmic: Central serous chorioretinopathy, exophthalmoses, glaucoma, increased intraocular pressure, posterior subcapsular cataracts, rare instances of blindness associated with periocular injections.

Other: Abnormal fat deposits, decreased resistance to infection, hiccups, increased or decreased motility and number of spermatozoa, injection site infections following non-sterile administration (see WARNINGS), malaise, moon face, weight gain.

OVERDOSAGE

Treatment of acute overdosage is by supportive and symptomatic therapy. For chronic overdosage in the face of severe disease requiring continuous steroid therapy, the dosage of the corticosteroid may be reduced only temporarily, or alternate day treatment may be introduced.

DOSAGE AND ADMINISTRATION

Because of possible physical incompatibilities, SOLU-CORTEF should not be diluted or mixed with other solutions.

Parenteral drug products should be inspected visually for particulate matter and discoloration prior to administration, whenever solution and container permit.

This preparation may be administered by intravenous injection, by intravenous infusion, or by intramuscular injection, the preferred method for initial emergency use being intravenous injection. Following the initial emergency period, consideration should be given to employing a longer acting injectable preparation or an oral preparation.

Therapy is initiated by administering SOLU-CORTEF Sterile Powder intravenously over a period of 30 seconds (e.g., 100 mg) to 10 minutes (e.g., 500 mg or more). In general, high dose corticosteroid therapy should be continued only until the patient's condition has stabilized, usually not beyond 48 hours to 72 hours. When high dose hydrocortisone therapy must be continued beyond 48 –72 hours, hypernatremia may occur. Under such circumstances, it may be desirable to replace SOLU-CORTEF with a corticoid such as methylprednisolone sodium succinate which causes little or no sodium retention.

The initial dose of SOLU-CORTEF Sterile Powder is 100 mg to 500 mg, depending on the specific disease entity being treated. However, in certain overwhelming, acute, life-threatening situations, administration in dosages exceeding the usual dosages may be justified and may be in multiples of the oral dosages.

This dose may be repeated at intervals of 2, 4, or 6 hours as indicated by the patient's response and clinical condition.

It Should Be Emphasized that Dosage Requirements Are Variable and Must Be Individualized on the Basis of the Disease Under Treatment and the Response of the Patient. After a favorable response is noted, the proper maintenance dosage should be determined by decreasing the initial drug dosage in small decrements at appropriate time intervals until the lowest dosage that maintains an adequate clinical response is reached. Situations that may make dosage adjustments necessary are changes in clinical status secondary to remissions or exacerbations in the disease process, the patient's individual drug responsiveness, and the effect of patient exposure to stressful situations not directly related to the disease entity under treatment. In this latter situation, it may be necessary to increase the dosage of the corticosteroid for a period of time consistent with the patient's condition. If after long-term therapy the drug is to be stopped, it is recommended that it be withdrawn gradually rather than abruptly.

In pediatric patients, the initial dose of hydrocortisone may vary depending on the specific disease entity being treated. The range of initial doses is 0.56 mg/kg/day to 8 mg/kg/day in three or four divided doses (20 mg/m^2bsa/day to 240 mg/m^2bsa/day). For the purpose of comparison, the following is the equivalent milligram dosage of the various glucocorticoids:

Cortisone, 25 | Triamcinolone, 4
Hydrocortisone, 20 | Paramethasone, 2
Prednisolone, 5 | Betamethasone, 0.75
Prednisone, 5 | Dexamethasone, 0.75
Methylprednisolone, 4

These dose relationships apply only to oral or intravenous administration of these compounds. When these substances or their derivatives are injected intramuscularly or into joint spaces, their relative properties may be greatly altered.

Preparation of Solutions:

100 mg Plain

For intravenous or intramuscular injection, prepare solution by aseptically adding not more than 2 mL of Bacteriostatic Water for Injection or Bacteriostatic Sodium Chloride Injection to the contents of one vial. For intravenous infusion, first prepare solution by adding not more than 2 mL of Bacteriostatic Water for Injection to the vial; this solution may then be added to 100 mL to 1,000 mL of the following: 5% dextrose in water (or isotonic saline solution or 5% dextrose in isotonic saline solution if patient is not on sodium restriction). From a microbiological point of view, unless the method of opening/reconstitution/dilution precludes the risk of microbial contamination, the product should be used immediately. If not used immediately, in use storage times and conditions are the responsibility of the user.

This product, like many other steroid formulations, is sensitive to heat. Therefore, it should not be autoclaved when it is desirable to sterilize the exterior of the vial.

DIRECTIONS FOR USING THE ACT-O-VIAL SYSTEM

1. Press down on plastic activator to force diluent into the lower compartment.
2. Gently agitate to effect solution.
3. Remove plastic tab covering center of stopper.
4. Sterilize top of stopper with a suitable germicide.
5. Insert needle squarely through center of stopper until tip is just visible. Invert vial and withdraw dose.

Further dilution is not necessary for intravenous or intramuscular injection. For intravenous infusion, first prepare solution as just described. The 100 mg solution may then be added to 100 mL to 1,000 mL of 5% dextrose in water (or isotonic saline solution or 5% dextrose in isotonic saline solution if patient is not on sodium restriction). The 250 mg solution may be added to 250 mL to 1,000 mL, the 500 mg solution may be added to 500 mL to 1,000 mL, and the 1,000 mg solution to 1,000 mL of the same diluents. In cases where administration of a small volume of fluid is desirable, 100 mg to 3,000 mg of SOLU-CORTEF may be added to 50 mL of the above diluents. The resulting solutions are stable for at least 4 hours and may be administered either directly or by IV piggyback.

When reconstituted as directed, pH's of the solutions range from 7 to 8.

HOW SUPPLIED

SOLU-CORTEF Sterile Powder is available in the following packages:

100 mg Plain—NDC 0009-0825-01
100 mg ACT-O-VIAL (Single-Dose Vial) | 250 mg ACT-O-VIAL (Single-Dose Vial)
2 mL—NDC 0009-0011-03 | 2 mL—NDC 0009-0013-05
25 × 2 mL—NDC 0009-0011-04 | 25 × 2 mL—NDC 0009-0013-06
500 mg ACT-O-VIAL (Single-Dose Vial)—NDC 0009-0016-12
1,000 mg ACT-O-VIAL (Single-Dose Vial)—NDC 0009-0005-01

STORAGE CONDITIONS

Store unreconstituted product at controlled room temperature 20°C to 25°C (68°F to 77°F).

Store reconstituted and/or further diluted solution at controlled room temperature 20°C to 25°C (68°F to 77°F) and protect from light. Use the reconstituted and/or further diluted solution within 12 hours of preparation. Use reconstituted/diluted solution only if it is clear. If kept at controlled room temperature unused reconstituted and/or further diluted solution should be discarded after 12 hours post preparation. If kept under refrigerated conditions, unused reconstituted and/or further diluted solution should be used in no more than 24 hours and any unused portion should be discarded after that time.

For medical information about SOLU‑CORTEF, please visit www.pfizermedinfo.com or call 1‑800‑438‑1985. This product's label may have been updated. For current full prescribing information please visit www.pfizer.com

LAB-0424-16.0
Revised July 2024

PRINCIPAL DISPLAY PANEL - 100 mg Vial Label

NDC 0009-0825-01
Single-Dose Vial

Solu-Cortef®
(hydrocortisone
sodium succinate
for injection, USP)

100 mg/vial

For intramuscular or intravenous use
Preservative-Free

Rx only

PRINCIPAL DISPLAY PANEL - 100 mg Vial Carton

NDC 0009-0825-01
Single-Dose Vial

Solu-Cortef®
(hydrocortisone
sodium succinate
for injection, USP)

100 mg/vial

For intramuscular or
intravenous use

Preservative-Free

Rx only

Pfizer Hospital

PRINCIPAL DISPLAY PANEL - 100 mg Single-Dose Vial Label

Single-Dose Vial
2 mL Act-O-Vial®
NDC 0009-0011-03

Solu-Cortef®
(hydrocortisone sodium
succinate for injection, USP)

100 mg/vial
Rx only

For intramuscular or intravenous use

PRINCIPAL DISPLAY PANEL - 100 mg Single-Dose Vial Carton

NDC 0009-0011-04
Contains 25 of NDC 0009-0011-03

25–2 mL Act-O-Vial® Systems
Single-Dose Vials

Solu-Cortef®
(hydrocortisone sodium
succinate for injection, USP)

100 mg/vial

For intramuscular or intravenous use

Preservative-Free
Rx only

Pfizer Hospital

PRINCIPAL DISPLAY PANEL - 250 mg Single-Dose Vial Label

Single-Dose Vial
2 mL Act-O-Vial®
NDC 0009-0013-05

Solu-Cortef®
(hydrocortisone sodium
succinate for injection, USP)

250 mg/vial

For intramuscular or intravenous use
Preservative-Free
Rx only

PRINCIPAL DISPLAY PANEL - 250 mg Single-Dose Vial Carton

NDC 0009-0013-05

Single-Dose Vial
2 mL Act-O-Vial®

Solu-Cortef®
(hydrocortisone
sodium succinate
for injection, USP)

250 mg/vial

For intramuscular or
intravenous use

Preservative-Free

Rx only

Pfizer Hospital

PRINCIPAL DISPLAY PANEL - 500 mg Single-Dose Vial Label

Single-Dose Vial
4 mL Act-O-Vial®
NDC 0009-0016-12

Solu-Cortef®
(hydrocortisone sodium
succinate for injection, USP)

500 mg/vial

For intramuscular or intravenous use

Preservative-Free
Rx only

PRINCIPAL DISPLAY PANEL - 500 mg Single-Dose Vial Carton

NDC 0009-0016-12

Single-Dose Vial
4 mL Act-O-Vial®

Solu-Cortef®
(hydrocortisone
sodium succinate
for injection, USP)

500 mg/vial

For intramuscular or
intravenous use

Preservative-Free

Rx only

Pfizer Hospital

PRINCIPAL DISPLAY PANEL - 1000 mg Single-Dose Vial Label

Single-Dose Vial
8 mL Act-O-Vial®
NDC 0009-0005-01

Solu-Cortef®
(hydrocortisone sodium
succinate for injection, USP)

1,000 mg/vial

For intramuscular or intravenous use
Preservative-Free
Rx only

PRINCIPAL DISPLAY PANEL - 1000 mg Single-Dose Vial Carton

NDC 0009-0005-01

Single-Dose Vial
8 mL Act-O-Vial®

Solu-Cortef®
(hydrocortisone
sodium succinate
for injection, USP)

1,000 mg/vial

For intramuscular or
intravenous use

Preservative-Free

Rx only

Pfizer Hospital